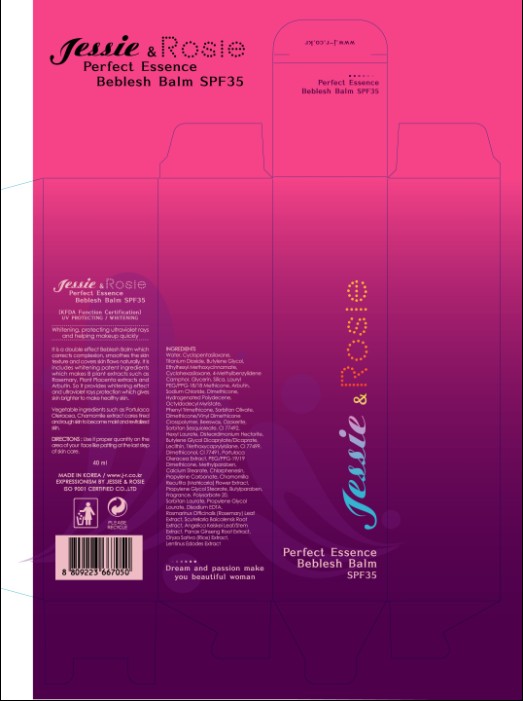 DRUG LABEL: J and R Perfect Essence Beblesh Balm (40mL)
NDC: 49715-001 | Form: CREAM
Manufacturer: WIZCOZ CORPORATION LTD
Category: otc | Type: HUMAN OTC DRUG LABEL
Date: 20091109

ACTIVE INGREDIENTS: TITANIUM DIOXIDE 3.6 mL/40 mL; OCTINOXATE 1.6 mL/40 mL

PACKAGE LABEL

Label1

ACTIVE INGREDIENT

Ingredients:

Water, Cyclopentasiloxane, Titatinum Dioxide, Butylene Glycol, Ethylhexyl Methoxycinnamate, Cyclohexasiloxane, 4-Methylbenzylidene Camphor, Glycerin, Silica, Lauryl PEG/PPG-18/18 Methicone, Arbutin, Sodium Chloride, Dimethicone, Hydrogenated Polydecene, Octyldodecyl Myristate, Phenyl Trimethicone, Sorbitan Olivate, Dimethicone/Vinyl Dimethicone Crosspolymer, Beeswax, Ozokerite, Sorbitan Sesquioleate, CI 11492, Hexyl Laurate, Disteardimonium Hectorite, Butylene Glycol Dicaprylate/Dicaprate, Lecithin, Triethoxycaprylylsilane, CI 77499, Dimethiconol, CI 77491, Portulaca Oleracea Extract, PEG/PPG-19/19 Dimethicone, Methylparaben, Calcium Stearate, Chlorphenesin, Propylene Carbonate, Chamomilla Recutita (Matricaria) Flower Extract, Propylene Glycol Stearate, Butylparaben, Fragrance, Polysorbate 20, Sorbitan Laurate, Propylene Glycol Laurate, Disodium EDTA, Rosmarinus Officinalis (Rosemary) Leaf Extract, Angelica Keiskei Leaf/Stem Extract, Panax Ginseng Root Extract, Oryza Sativa (Rice) Extract, Lentinus Edodes Extract

WHEN USING

DIRECTIONS: Use it proper quantity on the area of your face like patting at the last step of skin care.